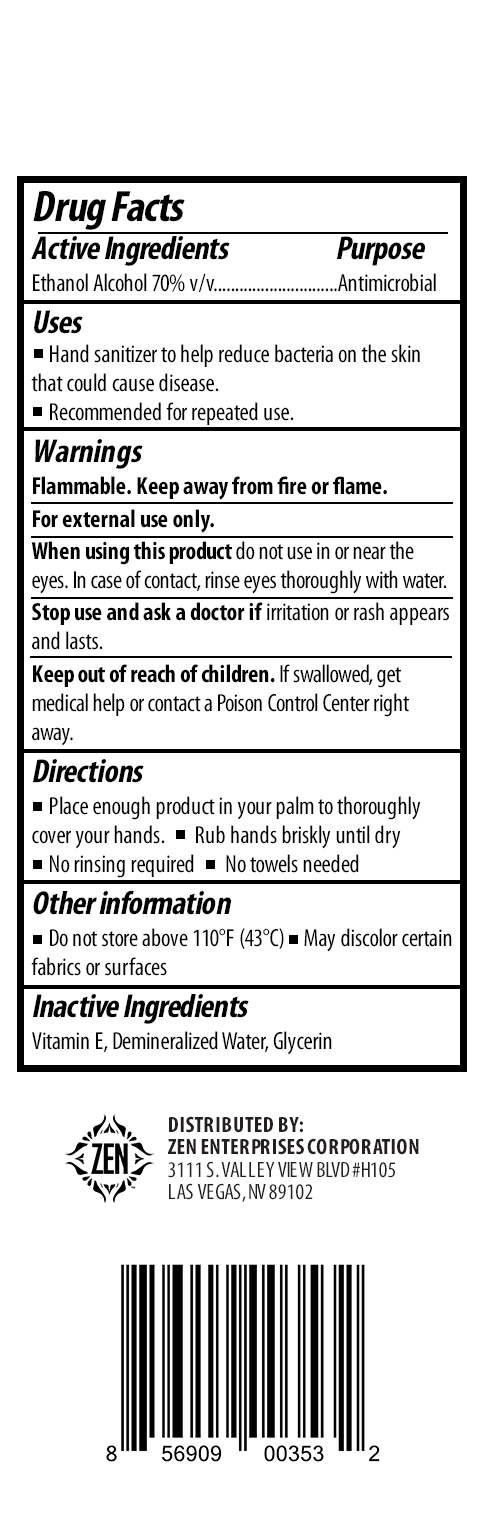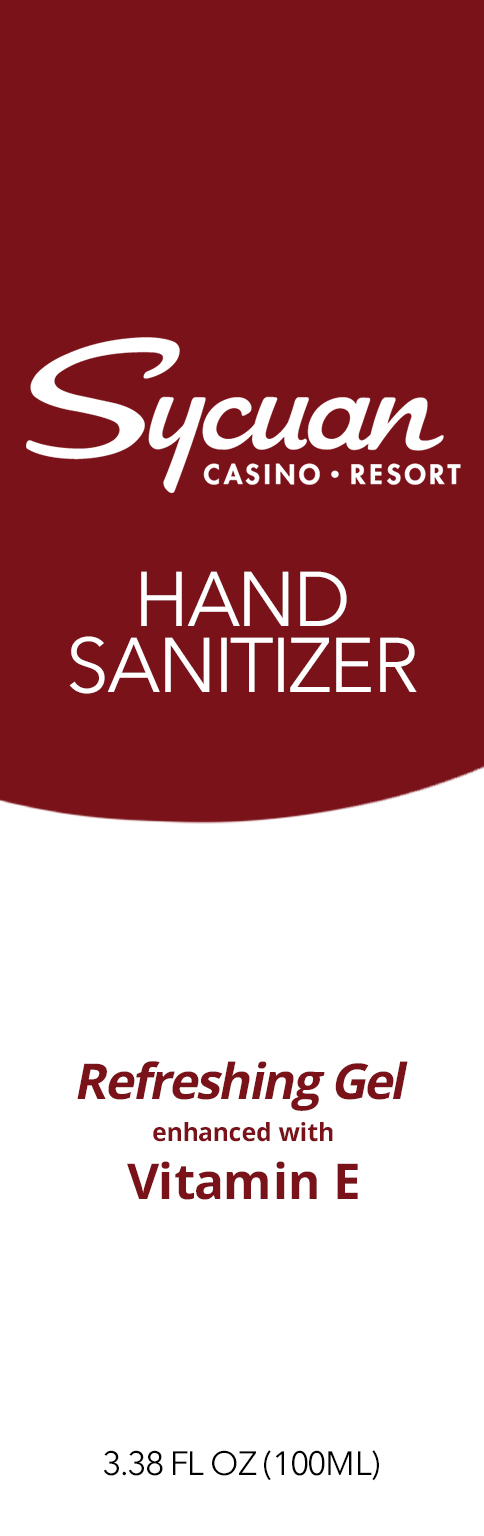 DRUG LABEL: Hand Sanitizer
NDC: 70146-012 | Form: GEL
Manufacturer: Dr.Sankunnis Ayurvedic Research Foundation Pvt Ltd
Category: otc | Type: HUMAN OTC DRUG LABEL
Date: 20200608

ACTIVE INGREDIENTS: ALCOHOL 70 mL/100 mL
INACTIVE INGREDIENTS: GLYCERIN; WATER; ALPHA-TOCOPHEROL

Hand Sanitizer

Active Ingredient(s)

Alcohol 70% v/v.

Purpose

Antimicrobial

Use

Hand Sanitizer to help reduce bacteria that potentially could cause disease. Recommended for repeated use

Warnings

For external use only. Flammable. Keep away from heat or flame

When using this product do not use in or near the eyes. In case of contact, rinse eyes thoroughly with water.

Stop use and ask a doctor if irritation or rash occurs. These may be signs of a serious condition.

Keep out of reach of children. If swallowed, get medical help or contact a Poison Control Center right away.

Directions

- Place enough product on hands to cover your hands. Rub hands briskly until dry.
- No rinsing required
- No towels needed

Other information

- Do not store above 110F (43C)
- May discolor certain fabrics or surfaces

Inactive ingredients

Vitamin E, Demineralized Water, Glycerin